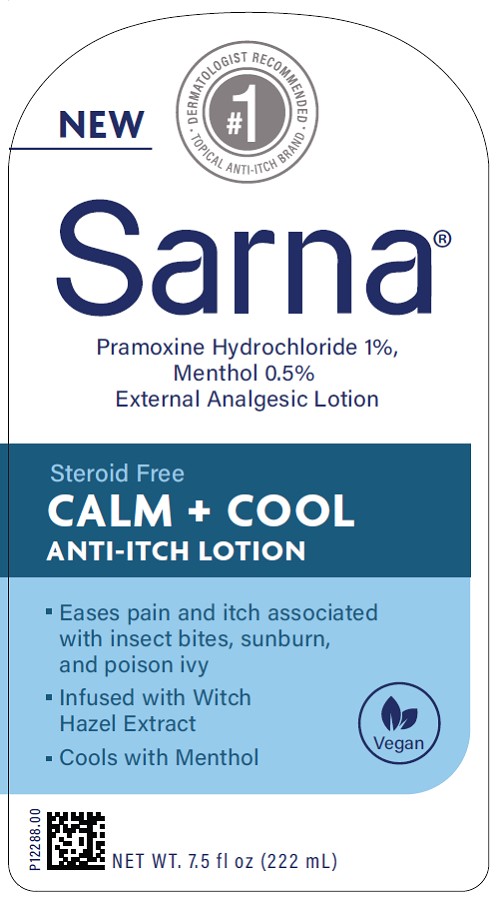 DRUG LABEL: Sarna
NDC: 0316-0234 | Form: LOTION
Manufacturer: Crown Laboratories, Inc
Category: otc | Type: HUMAN OTC DRUG LABEL
Date: 20260112

ACTIVE INGREDIENTS: MENTHOL 0.5 mg/1000 mL; PRAMOXINE HYDROCHLORIDE 10 mg/1000 mL
INACTIVE INGREDIENTS: STEARIC ACID; PEG-100 STEARATE; BENZYL ALCOHOL; CAPRYLYL GLYCOL; TOCOPHEROL; WATER; CARBOMER HOMOPOLYMER TYPE C; PENTYLENE GLYCOL; GLYCERYL MONOSTEARATE; BUTYLENE GLYCOL; CETYL ALCOHOL; ETHYLHEXYLGLYCERIN; ISOPROPYL MYRISTATE; HAMAMELIS VIRGINIANA LEAF; ALOE VERA LEAF; PEG-8 STEARATE; DIMETHICONE; GLYCERIN; PALMITIC ACID; SODIUM HYDROXIDE; YEAST .BETA.-D-GLUCAN

Sarna Calm + Cool

Active Ingredients

Menthol 0.5%

Pramoxine Hydrochloride 1%

Purpose

External analgesic

Uses

- for the temporary relief of pain and itching associated with minor burns, sunburn, minor cuts, scrapes, insect bites, minor skin irritations and rashes due to poison ivy, poison oak, or poison sumac

Warnings

For external use only.

Do not use

- in the eyes or nose
- over large areas of the body
- for prolonged periods

When using this product

- avoid contact with the eyes.
- if condition worsens, or if symptoms persist for more than 7 days or clear up and occur again within a few days, discontinue use of this product and consult a doctor.

Stop use and ask a doctor if

- redness, irritation, swelling, or pain persists or increases.

Keep out of reach of children.

If swallowed, get medical help or contact a Poison Control Center right away.

Directions

- to open, hold cap and turn pump clockwise.
- Adults and children 2 years of age and older: Apply to affected area not more than 3 to 4 times daily. Children under 2 years of age: do not use, consult a doctor.

Other information

- store at 20°–25°C (68°–77°F) [see USP Controlled Room Temperature]

Inactive ingredients

Aloe Barbadensis Leaf Juice, Benzyl Alcohol, Beta-Glucan, Butylene Glycol, C12-18 Alkanoyl Glycerin/Sebacic Acid Copolymer, Caprylyl Glycol, Carbomer, Cetyl Alcohol, Dimethicone, Ethylhexylglycerin, Glycerin, Glyceryl Stearate, Hamamelis Virginiana (Witch Hazel) Leaf Extract, Isopropyl Myristate, Palmitic Acid, PEG-100 Stearate, PEG-8 Stearate, Pentylene Glycol, Sodium Hydroxide, Stearic Acid, Tocopherol, Water

Questions?

call 1-833-279-6522

Sarna Calm + Cool Principal Display Panel

#1 DERMATOLOGIST RECOMMENDED TOPICAL ANTI-ITCH BRAND

Sarna

Pramoxine Hydrochloride 1%

Menthol 0.5%

External Analgesic Lotion

Steroid Free

CALM + COOL

ANTI-ITCH LOTION

Eases pain and itch associated with insect bites, sunburn, and poison ivy

Infused with Witch Hazel Extract

Cools with Menthol

NET WT. 7.5fl oz (222 ml)

P12288.00